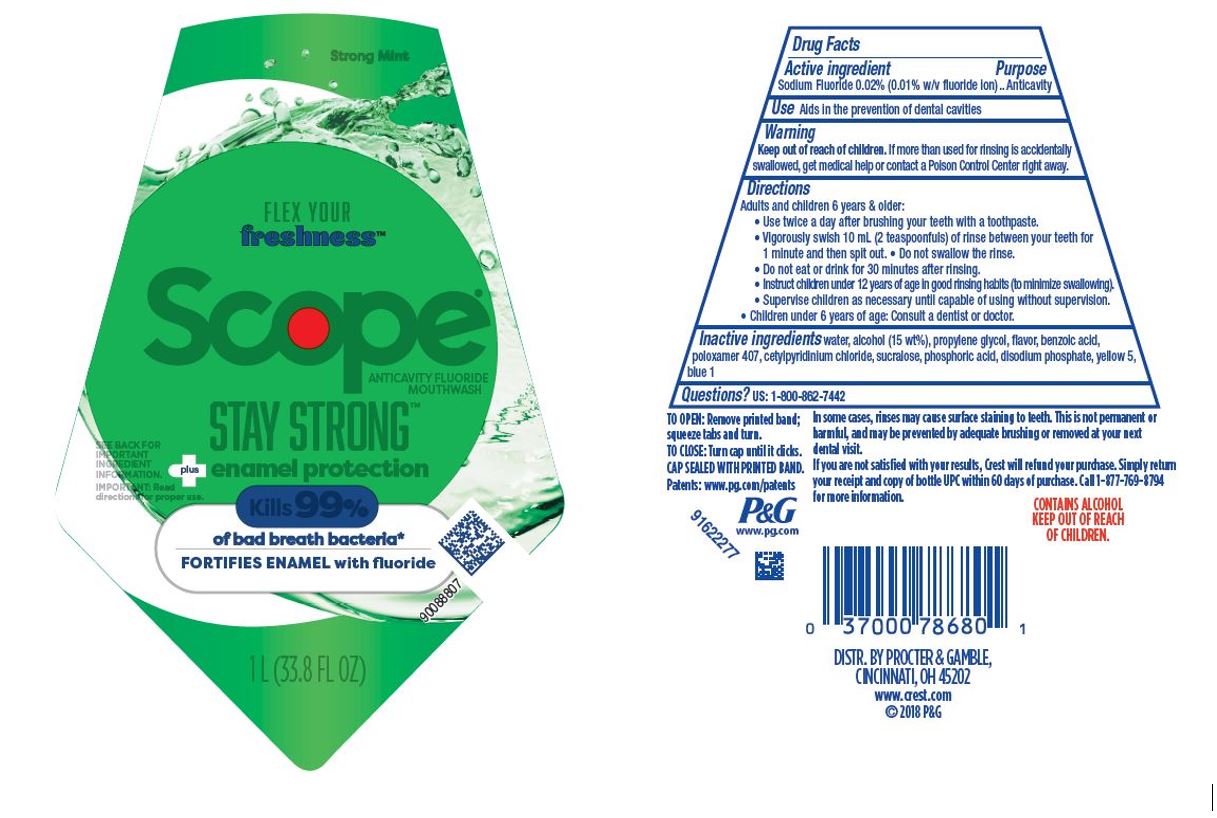 DRUG LABEL: Scope
NDC: 69423-859 | Form: RINSE
Manufacturer: The Procter & Gamble Manufacturing Company
Category: otc | Type: HUMAN OTC DRUG LABEL
Date: 20250731

ACTIVE INGREDIENTS: SODIUM FLUORIDE 0.02 mg/1 mL
INACTIVE INGREDIENTS: CETYLPYRIDINIUM CHLORIDE; BENZOIC ACID; PHOSPHORIC ACID; WATER; SODIUM PHOSPHATE, DIBASIC, ANHYDROUS; BASIC BLUE 1; BASIC YELLOW 5; PROPYLENE GLYCOL; POLOXAMER 407; ALCOHOL; SUCRALOSE

Scope Stay Strong

Drug Facts

Active ingredient

Sodium Fluoride 0.02% (0.01% w/v fluoride ion)

Purpose

Anticavity

Use

Aids in the prevention of dental cavities

Warning

Keep out of reach of children. If more than used for rinsing is accidentally swallowed, get medical help or contact a Poison Control Center right away.

Directions

- Adults and children 6 years & older: Use twice a day after brushing your teeth with a toothpaste.
- Vigorously swish the 10 mL (2 teaspoonfuls) of rinse between your teeth for 1 minute and then spit out.
- Do not swallow the rinse.
- Do not eat or drink for 30 minutes after rinsing.
- Instruct children under 12 years of age in good rinsing habits (to minimize swallowing).
- Supervise children as necessary until capable of using without supervision.
- Children under 6 years of age: Consult a dentist or doctor.

Inactive ingredients

water, glycerin, propylene glycol, polysorbate 80, benzoic acid, flavor, saccharin, sodium benzoate, phosphoric acid, disodium phosphate, yellow 5, blue 1

Questions?

1-800-862-7442

DISTR. BY PROCTER & GAMBLE,
CINCINNATI, OH 45202

PRINCIPAL DISPLAY PANEL - 1000 mL Bottle Label

Strong Mint

FLEX YOUR

freshness™

Scope®

ANTICAVITY FLUORIDE MOUTHWASH

STAY STRONG™

plus enamel protection

SEE BACK FOR IMPORTANT INGREDIENT INFORMATION

IMPORTANT: Read directions for proper use.

Kills 99%

of bad breath bacteria*

FORTIFIES ENAMEL with fluoride

1L (33.8 FL OZ)